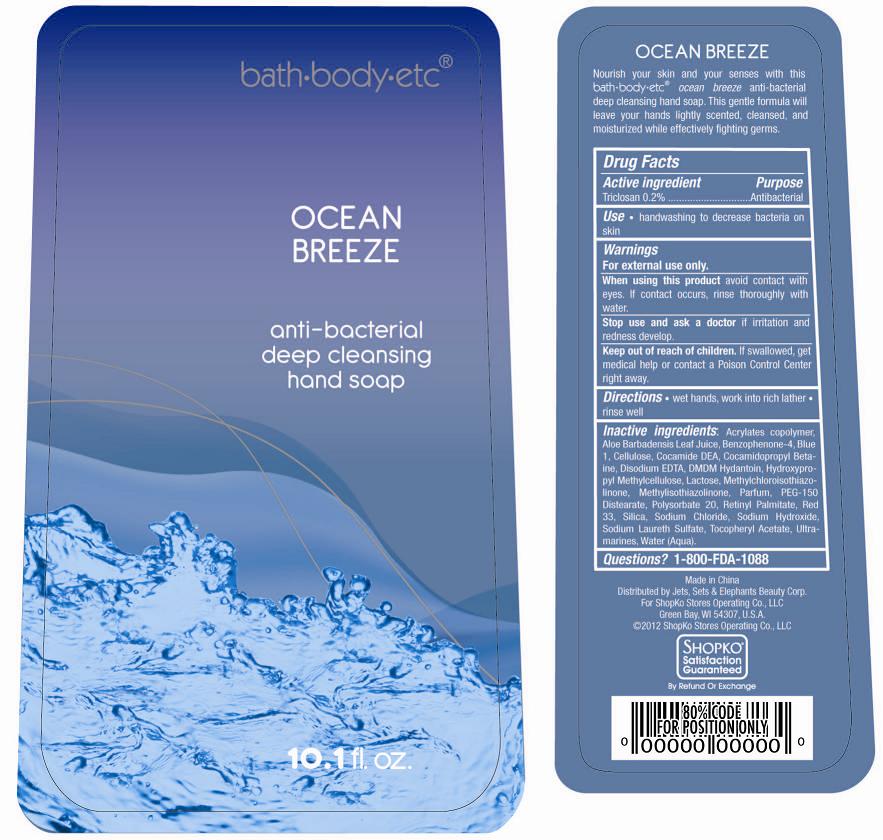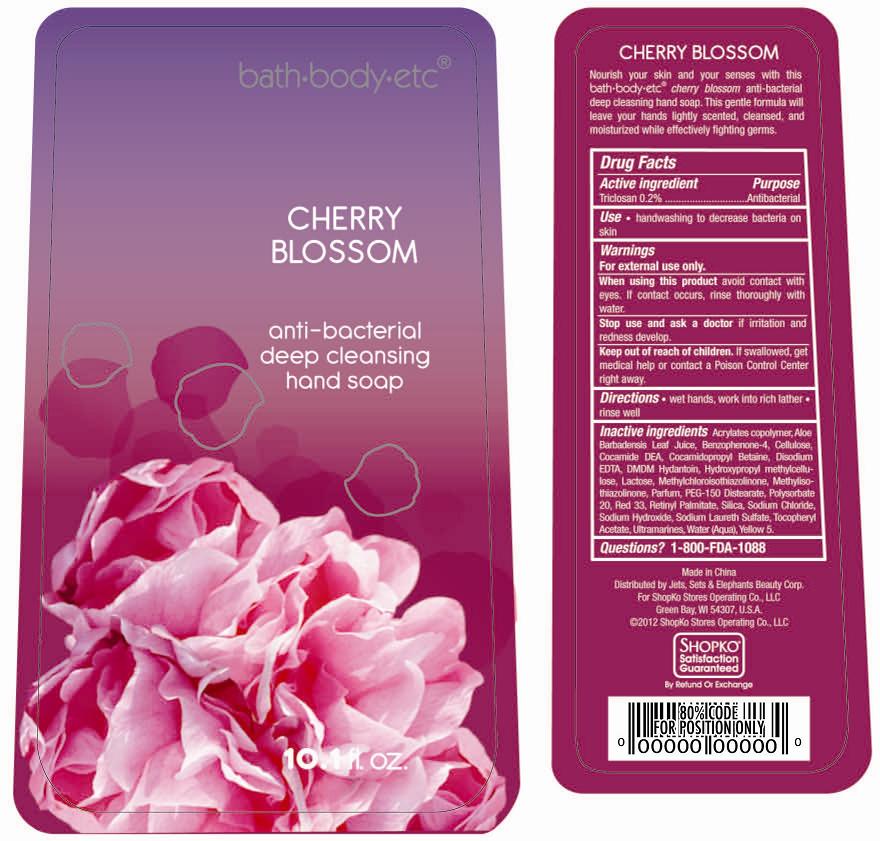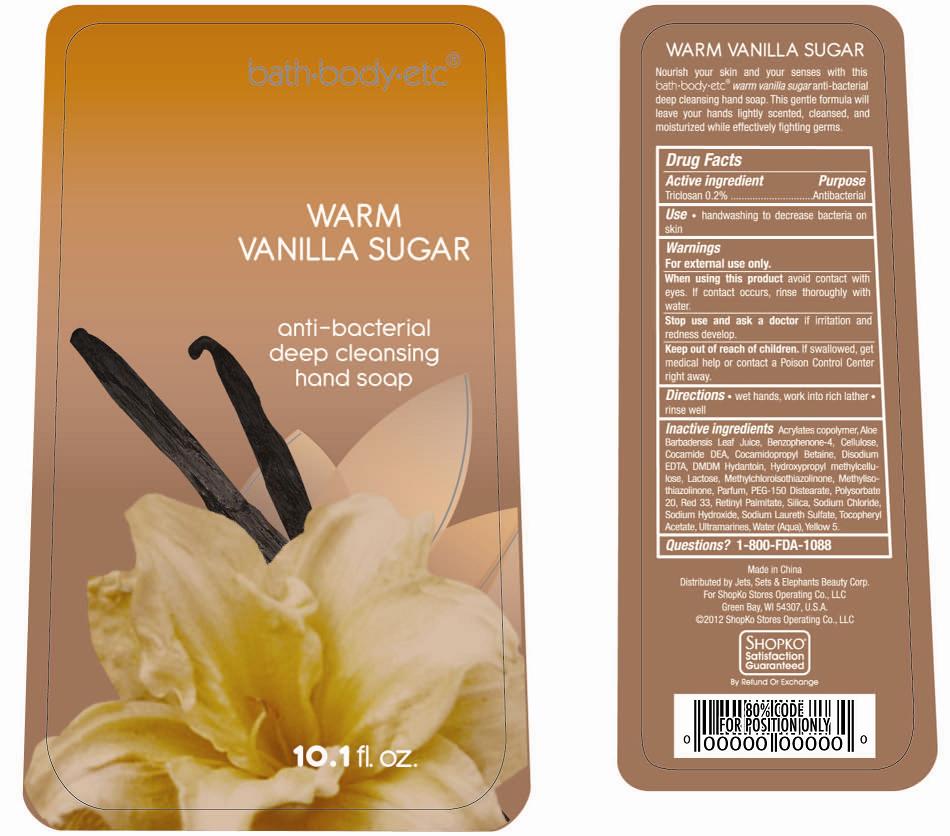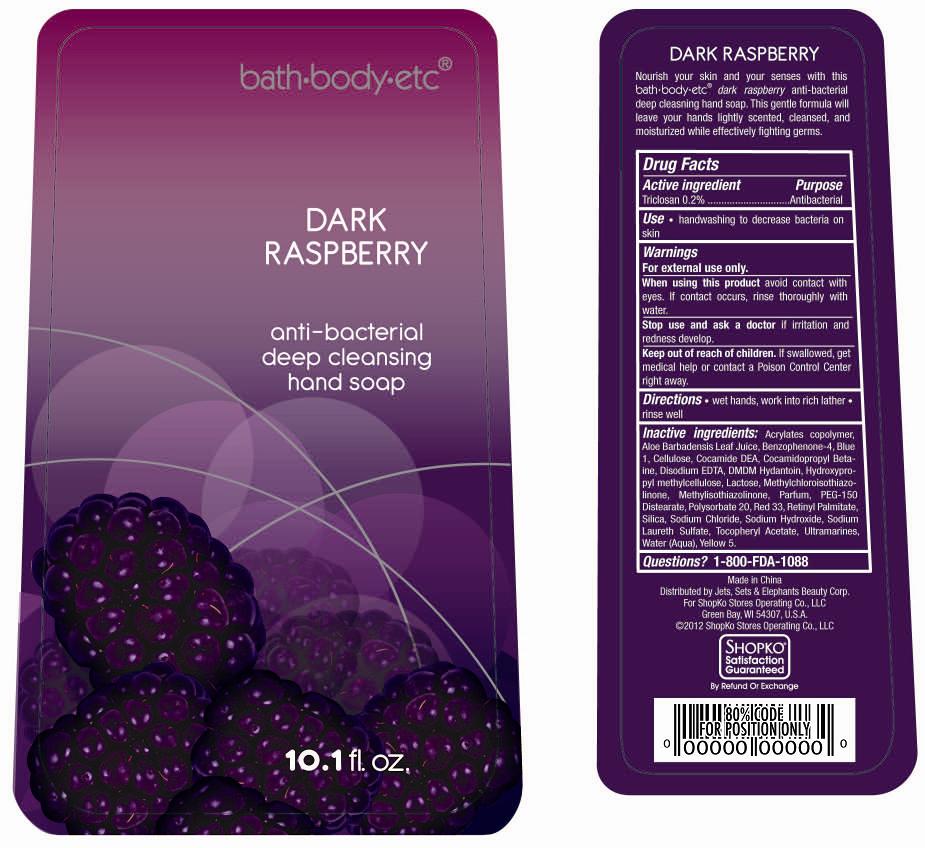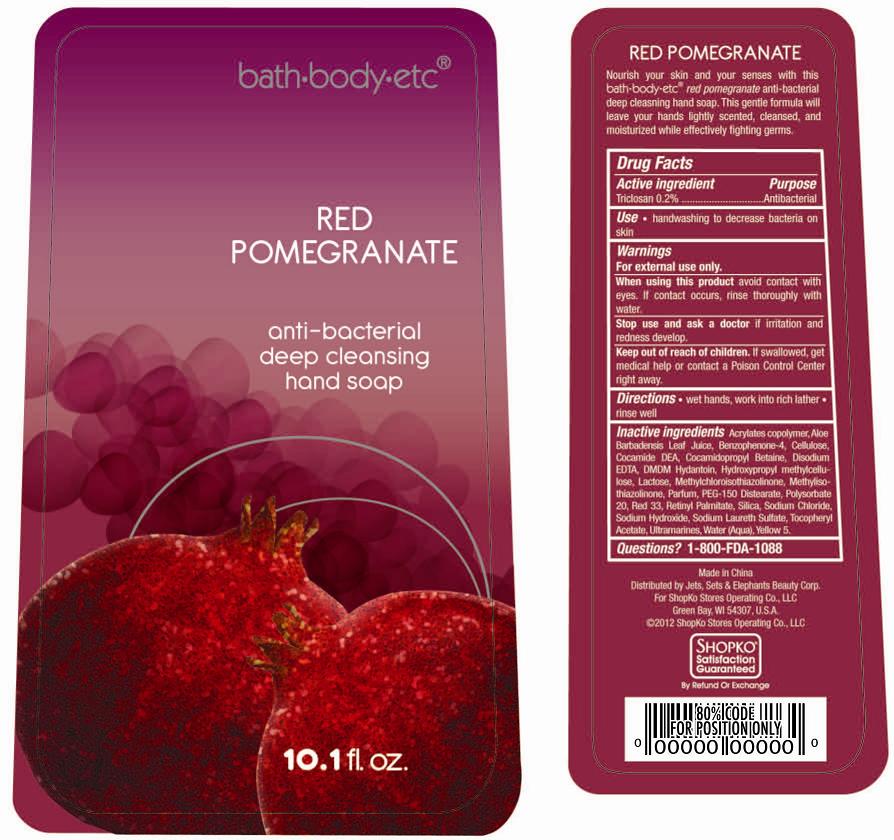 DRUG LABEL: Shopko Antibacterial Deep Cleansing Hand
NDC: 50988-450 | Form: GEL
Manufacturer: Jets, Sets, & Elephants Beauty Corp.
Category: otc | Type: HUMAN OTC DRUG LABEL
Date: 20120628

ACTIVE INGREDIENTS: TRICLOSAN 0.2 mL/100 mL
INACTIVE INGREDIENTS: WATER; SODIUM LAURETH SULFATE; COCAMIDOPROPYL BETAINE; COCO DIETHANOLAMIDE; POLYSORBATE 20; SODIUM CHLORIDE; SILICON DIOXIDE; PEG-150 DISTEARATE; DMDM HYDANTOIN; LACTOSE; CELLULOSE, MICROCRYSTALLINE; HYPROMELLOSE 2208 (100 MPA.S); .ALPHA.-TOCOPHEROL ACETATE, D-; ULTRAMARINE BLUE; ALOE VERA LEAF; METHYLISOTHIAZOLINONE; METHYLCHLOROISOTHIAZOLINONE; SODIUM HYDROXIDE; EDETATE CALCIUM DISODIUM ANHYDROUS; SULISOBENZONE; VITAMIN A PALMITATE; FD&C BLUE NO. 1; D&C RED NO. 33

bath+body+etc® antibacterial deep cleansing hand soap - Ocean Breeze, Cherry Blossom, Warm Vanilla Sugar, Dark Raspberry, and Red Pomegranate

Active ingredient

Triclosan 0.2%

Purpose

Antibacterial

Uses

- handwashing to decrease bacteria on skin

Warnings

For external use only.

When using this product

Avoid contact with eyes. If contact occurs, rinse thoroughly with water.

Stop use and ask a doctor

If irritation and redness develop.

Keep out of reach of children.

If swallowed, get medical help or contact a Poison Control Center right away.

Directions

- wet hands, work into rich lather
- rinse well

Inactive Ingredients

Ocean Breeze

Acrylates copolymer, Aloe Barbadensis Leaf Juice, Benzophenone-4, Blue 1, Cellulose, Cocamide DEA, Cocamidopropyl Betaine, Disodium EDTA, DMDM Hydantoin, Hydroxypropyl methylcellulose, Lactose, Methylchloroisothiazolinone, Methylisothiazolinone, Parfum, PEG-150 Distearate, Polysorbate 20, Retinyl Palmitate, Red 33, Silica, Sodium Chloride, Sodium Hydroxide, Sodium Laureth Sulfate, Tocopheryl Acetate, Ultramarines, Water (Aqua).

Cherry Blossom

Acrylates copolymer, Aloe Barbadensis Leaf Juice, Benzophenone-4, Cellulose, Cocamide DEA, Cocamidopropyl Betaine, Disodium EDTA, DMDM Hydantoin, Hydroxypropyl methylcellulose, Lactose, Methylchloroisothiazolinone, Methylisothiazolinone, Parfum, PEG-150 Distearate, Polysorbate 20, Red 33, Retinyl Palmitate, Silica, Sodium Chloride, Sodium Hydroxide, Sodium Laureth Sulfate, Tocopheryl Acetate, Ultramarines, Water (Aqua), Yellow 5.

Warm Vanilla Sugar

Acrylates copolymer, Aloe Barbadensis Leaf Juice, Benzophenone-4, Cellulose, Cocamide DEA, Cocamidopropyl Betaine, Disodium EDTA, DMDM Hydantoin, Hydroxypropyl methylcellulose, Lactose, Methylchloroisothiazolinone, Methylisothiazolinone, Parfum, PEG-150 Distearate, Polysorbate 20, Red 33, Retinyl Palmitate, Silica, Sodium Chloride, Sodium Hydroxide, Sodium Laureth Sulfate, Tocopheryl Acetate, Ultramarines, Water (Aqua), Yellow 5.

Dark Raspberry

Acrylates copolymer, Aloe Barbadensis Leaf Juice, Benzophenone-4, Blue 1, Cellulose, Cocamide DEA, Cocamidopropyl Betaine, Disodium EDTA, DMDM Hydantoin, Hydroxypropyl methylcellulose, Lactose, Methylchloroisothiazolinone, Methylisothiazolinone, Parfum, PEG-150 Distearate, Polysorbate 20, Red 33, Retinyl Palmitate, Silica, Sodium Chloride, Sodium Hydroxide, Sodium Laureth Sulfate, Tocopheryl Acetate, Ultramarines, Water (Aqua), Yellow 5.

Red Pomegranate

Acrylates copolymer, Aloe Barbadensis Leaf Juice, Benzophenone-4, Cellulose, Cocamide DEA, Cocamidopropyl Betaine, Disodium EDTA, DMDM Hydantoin, Hydroxypropyl methylcellulose, Lactose, Methylchloroisothiazolinone, Methylisothiazolinone, Parfum, PEG-150 Distearate, Polysorbate 20, Red 33, Retinyl Palmitate, Silica, Sodium Chloride, Sodium Hydroxide, Sodium Laureth Sulfate, Tocopheryl Acetate, Ultramarines, Water (Aqua), Yellow 5.

Questions?

1-800-FDA-1088

Package/Label Principal Display Panel - Bottle Label

bath+body+etc®

Ocean Breeze

antibacterial

deep cleansing

hand soap

10.1 fl oz

Made in China

Distributed by Jets, Sets & Elephants Beauty Corp.

For Shopko Stores Operating Co., LLC

Green Bay, WI 54307, U.S.A.

©2012 Shopko Stores Operating Co., LLC

Ocean Breeze Bottle Label

Package/Label Principal Display Panel - Bottle Label

bath+body+etc®

Cherry Blossom

antibacterial

deep cleansing

hand soap

10.1 fl oz

Made in China

Distributed by Jets, Sets & Elephants Beauty Corp.

For Shopko Stores Operating Co., LLC

Green Bay, WI 54307, U.S.A.

©2012 Shopko Stores Operating Co., LLC

Cherry Blossom Bottle Label

Package/Label Principal Display Panel - Bottle Label

bath+body+etc®

Warm Vanilla Sugar

antibacterial

deep cleansing

hand soap

10.1 fl oz

Made in China

Distributed by Jets, Sets & Elephants Beauty Corp.

For Shopko Stores Operating Co., LLC

Green Bay, WI 54307, U.S.A.

©2012 Shopko Stores Operating Co., LLC

Warm Vanilla Sugar Bottle Label

Package/Label Principal Display Panel - Bottle Label

bath+body+etc®

Dark Raspberry

antibacterial

deep cleansing

hand soap

10.1 fl oz

Made in China

Distributed by Jets, Sets & Elephants Beauty Corp.

For Shopko Stores Operating Co., LLC

Green Bay, WI 54307, U.S.A.

©2012 Shopko Stores Operating Co., LLC

Dark Raspberry Bottle Label

Package/Label Principal Display Panel - Bottle Label

bath+body+etc®

Red Pomegranate

antibacterial

deep cleansing

hand soap

10.1 fl oz

Made in China

Distributed by Jets, Sets & Elephants Beauty Corp.

For Shopko Stores Operating Co., LLC

Green Bay, WI 54307, U.S.A.

©2012 Shopko Stores Operating Co., LLC

Red Pomegranate Bottle Label